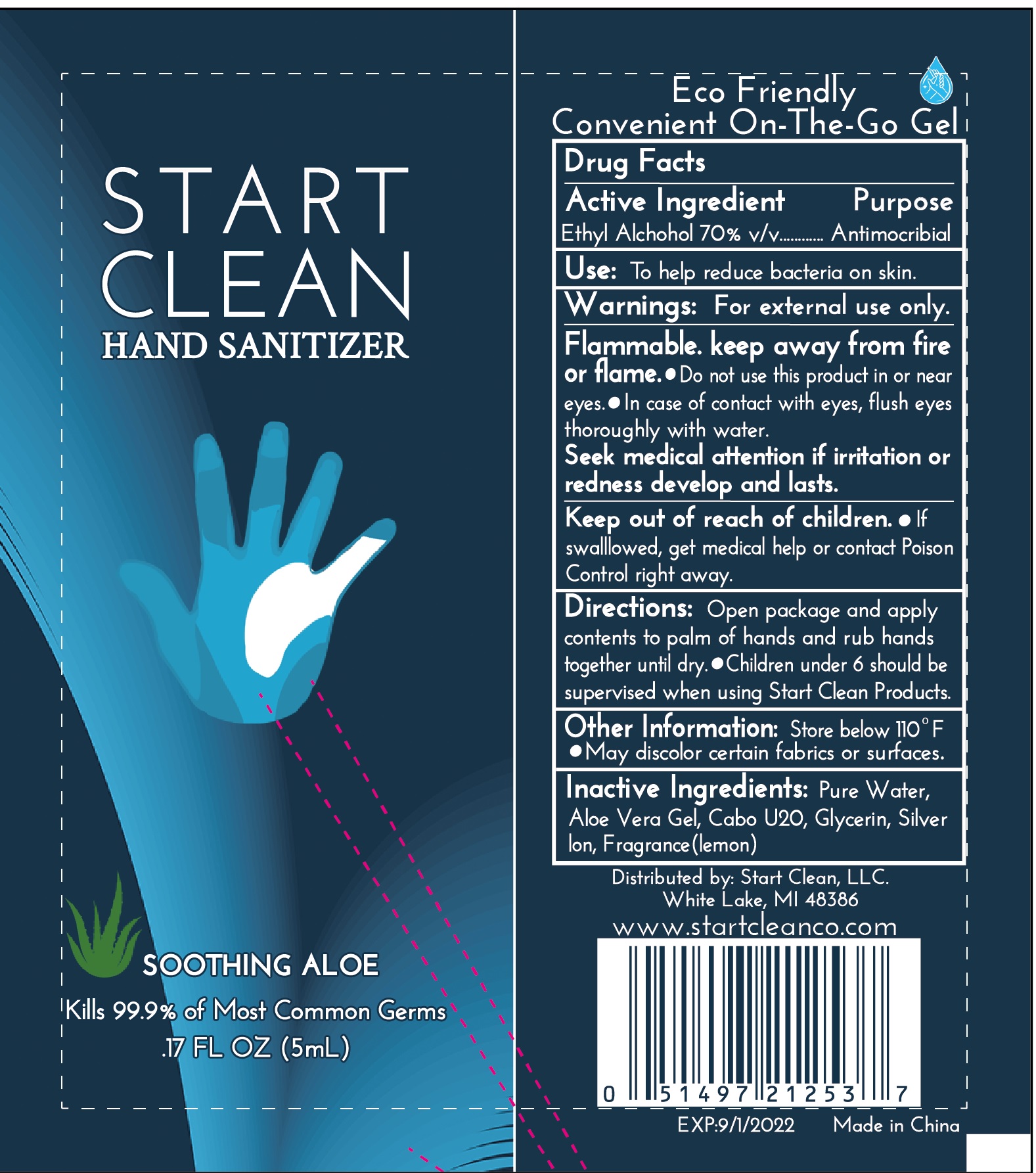 DRUG LABEL: Start Clean hand sanitizer
NDC: 71734-332 | Form: LIQUID
Manufacturer: JIANGMEN SHUIZIRUN SANITARY ARTICLES CO., LTD.
Category: otc | Type: HUMAN OTC DRUG LABEL
Date: 20201007

ACTIVE INGREDIENTS: ALCOHOL 70 mL/100 mL
INACTIVE INGREDIENTS: GLYCERIN; WATER; ALOE VERA LEAF

Drug Fact

Active Ingredient

Ethly Alcohol 70%

Purpose

Antimocribial

USE:

To help reduce bacteria on skin.

Warnings

For external use only.

Flammable. Keep away from fire or flame.

- Do not use this product in or near eyes.
- In case of contact with eyes,flush eyes thoroughly with water.
- Seek medical attention if irritation or redness develop and the lasts.

Other information

Store below 110 ℉. May discolor certain fabrics or surfaces.

Keep out of reach of children. If swalllowed ,get medical help or contact poison Control right away.

Directions

- Open package and apply contents to palm of hands and rub hands together until dry
- Children under 6 should be supervised when using Start Clean Products.

Inactive Ingredients

Purified water, Glycerine, Aloe Vera Gel, Glycerin, Silver ion, lemon fragrance.